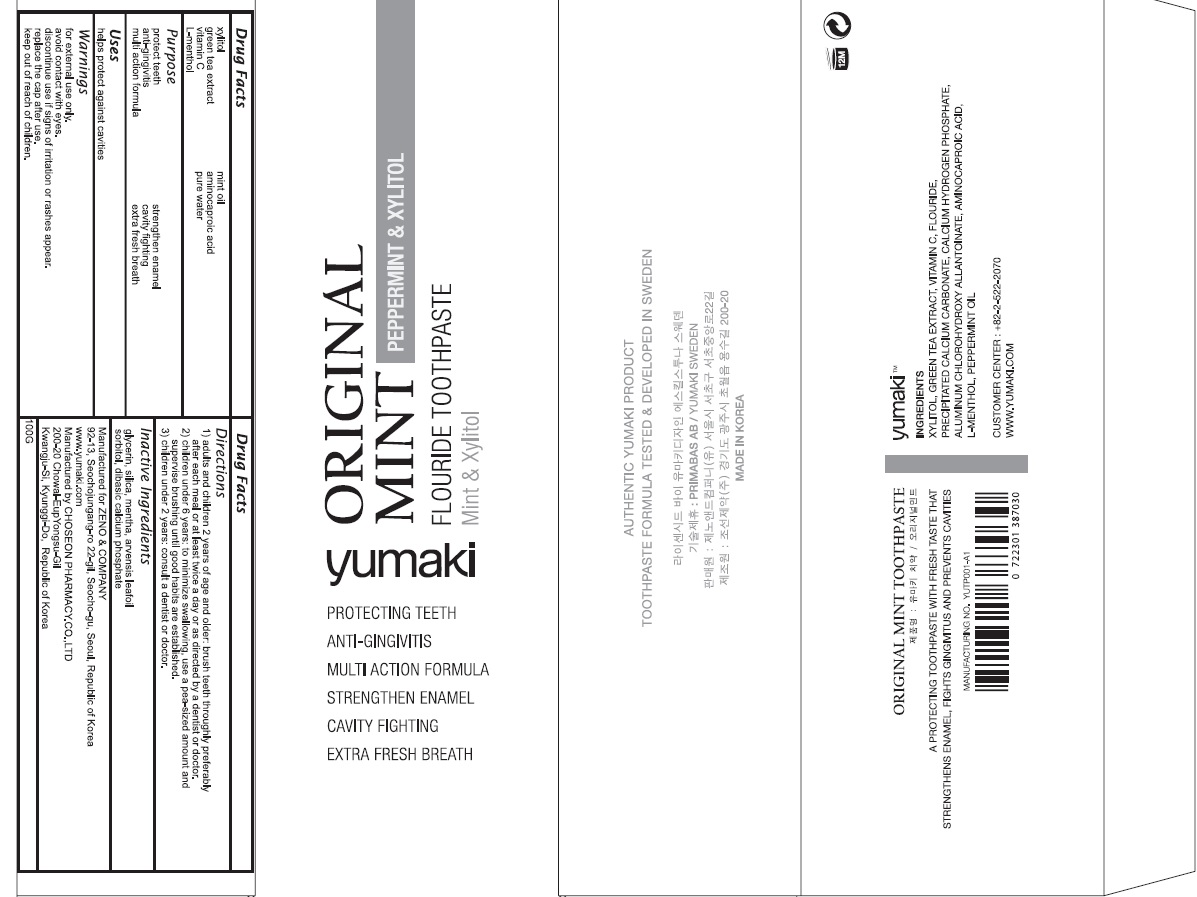 DRUG LABEL: YUMAKI ORIGINAL MINT TOOTH
NDC: 71746-010 | Form: PASTE, DENTIFRICE
Manufacturer: Jeno And Company
Category: otc | Type: HUMAN OTC DRUG LABEL
Date: 20171207

ACTIVE INGREDIENTS: XYLITOL 0.1 g/100 g; GREEN TEA LEAF 0.1 g/100 g; ASCORBIC ACID 0.005 g/100 g; LEVOMENTHOL 0.1 g/100 g; PEPPERMINT OIL 0.05 g/100 g; AMINOCAPROIC ACID 0.05 g/100 g; WATER 45.15 g/100 g
INACTIVE INGREDIENTS: Glycerin

ACTIVE INGREDIENT

Active ingredients: Xylitol 0.1%, Green tea Extract 0.1%, Vitamin C 0.005%, L-Menthol 0.1%, Mint oil 0.05%, Aminocaproic Acid 0.02%, Pure water 45.15%

INACTIVE INGREDIENT

Inactive ingredients: GLYCERIN, SILICA, MENTHA, ARVENSIS LEAFOIL SORBITOL, DIBASIC CALCIUM PHOSPHATE

PURPOSE

Purpose: Protect Teeth, Anti-Gingivitis, Multi Action Formula, Strengthen Enamel, Cavity Fighting, Extra Fresh Breath

WARNINGS

Warnings: For external use only. Avoid contact with eyes. Discontinue use if signs of irritation or rashes appear. Replace the cap after use. Keep Out of Reach of Children.

KEEP OUT OF REACH OF CHILDREN

Uses

Uses: Helps protect against cavities

Directions

1) Adults and children 2 years of age and older: Brush teeth throughly preferably after each meal or at least twice a day or as directed by a dentist or doctor.

2) Children under 6 years: To minimize swallowing, use a pea-sized amount and supervise brushing until good habits are established.

3) Children under 2 years: Consult a dentist or doctor.